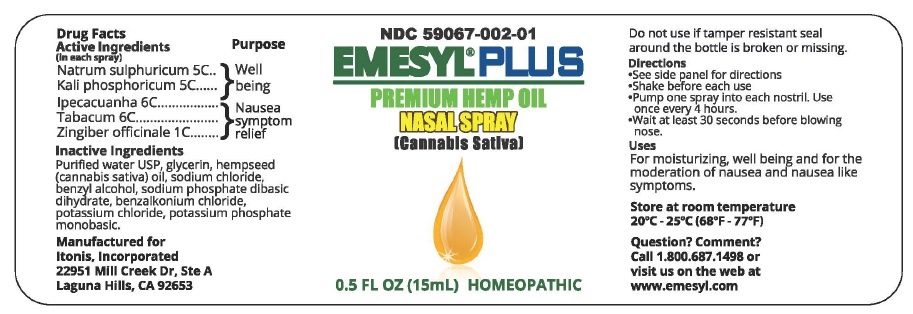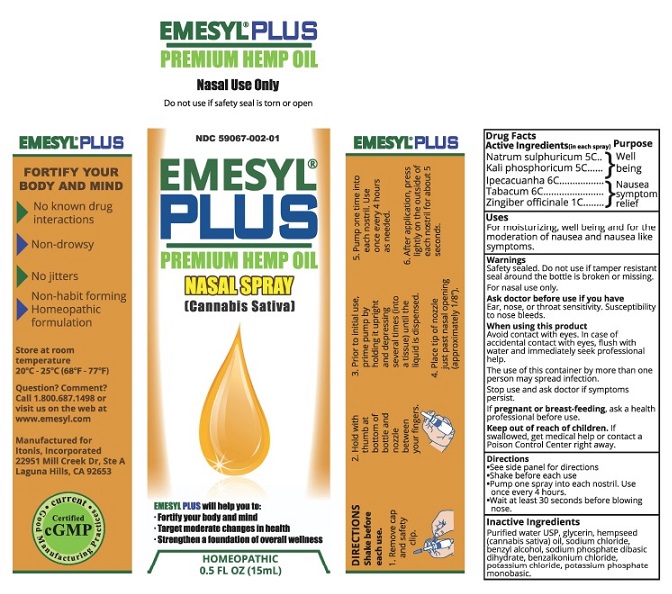 DRUG LABEL: Emesyl Plus
NDC: 59067-002 | Form: SPRAY
Manufacturer: Itonis Inc.
Category: homeopathic | Type: HUMAN OTC DRUG LABEL
Date: 20180607

ACTIVE INGREDIENTS: SODIUM SULFATE 5 [hp_C]/15 mL; DIBASIC POTASSIUM PHOSPHATE 5 [hp_C]/15 mL; IPECAC 6 [hp_C]/15 mL; TOBACCO LEAF 6 [hp_C]/15 mL; GINGER 1 [hp_C]/15 mL
INACTIVE INGREDIENTS: WATER; GLYCERIN; CANNABIS SATIVA SEED OIL; SODIUM CHLORIDE; BENZYL ALCOHOL; SODIUM PHOSPHATE DIBASIC DIHYDRATE; BENZALKONIUM CHLORIDE; POTASSIUM CHLORIDE; POTASSIUM PHOSPHATE, MONOBASIC

Emesyl® Plus

Drug Facts

Active Ingredients

Natrum sulphuricum ... 5C
Kali phosphoricum ..... 5C

Ipecacuanha ............... 6C
Tabacum..................... 6C
Zingiber officinale ..... 1C

Purpose

Well being

Nausea symptom relief

Uses
For moisturizing, well being and for the
moderation of nausea and nausea like
symptoms.

Warnings
Safety sealed. Do not use if tamper resistant
seal around the bottle is broken or missing.

For nasal use only.

Ask doctor before use if you have
Ear, nose, or throat sensitivity. Susceptibility
to nose bleeds.

When using this product
Avoid contact with eyes. In case of
accidental contact with eyes, flush with
water and immediately seek professional
help.

The use of this container by more than one
person may spread infection.

Stop use and ask doctor if symptoms
persist.

If pregnant or breast-feeding, ask a health
professional before use.

Keep out of reach of children. If
swallowed, get medical help or contact a
Poison Control Center right away.

Directions
●See side panel for directions
●Shake before each use
●Pump one spray into each nostril. Use
once every 4 hours.
●Wait at least 30 seconds before blowing
nose.

Inactive Ingredients
Purified water USP, glycerin, hempseed
(cannabis sativa) oil, sodium chloride,
benzyl alcohol, sodium phosphate dibasic
dihydrate, benzalkonium chloride,
potassium chloride, potassium phosphate
monobasic.

PACKAGE LABEL

EMESYL® PLUS
PREMIUM HEMP Oil

Nasal Use Only

Do not use if safety seal is torn or open

NDC 59067·002·01

EMESYL® PLUS
PREMIUM HEMP Oil
NASAL SPRAY
[Cannabis Sativa)

EMESYL PLUS will help you to:
●Fortify your body and mind
●Target moderate changes in health
●Strengthen a foundation of overall wellness

HOMEOPATHIC
0.5 FL OZ (15mL)

EMESYL® PLUS

FORTIFY YOUR
BODY AND MIND

► No known drug
Interactions

► Non-drowsy

► No jitters

► Non-habit forming
Homeopathic formulation

Store at room
temperature
20°C - 25°C (68°F -77°F)

Question? Comment?
Call 1.800.687.1498 or
visit us on the web at
www.emesyl.com

Manufactured for
Itonis, Incorporated
22951 Mill Creek Dr, Ste A
Laguna Hills, CA 92653

Certified
cGMP
●current● Good Manufacturing Practices

EMESYL® PLUS

DIRECTIONS
Shake before each use.

1. Remove cap and safety tip.

2. Hold with thumb at bottom
of bottle and nozzle between
your fingers.

3. Prior to initial use, prime pump
by holding it upright and depressing
several times (into a tissue) until
the liquid is dispensed.

4. Place tip of nozzle just past nasal
opening (approximately 1/8”).

5. Pump one time into each nostril.
Use once every 4 hours as needed.

6. After application, press on the
outside of each nostril for
about 5 seconds.

Drug Facts
Active Ingredients(in each spray) Purpose

Natrum sulphuricum 5C................... Well
Kali phosphoricum 5C..................... being

Ipecacuanha 6C........................... Nausea
Tabacum 6C.:............................. symptom
Zingiber officinale 1C..................... relief

Uses
For moisturizing, well being and for the
moderation of nausea and nausea like
symptoms.

Warnings
Safety sealed. Do not use if tamper resistant
seal around the bottle is broken or missing.

For nasal use only.

Ask doctor before use if you have
Ear, nose, or throat sensitivity. Susceptibility
to nose bleeds.

When using this product
Avoid contact with eyes. In case of
accidental contact with eyes, flush with
water and immediately seek professional
help.

The use of this container by more than one
person may spread infection.

Stop use and ask doctor if symptoms
persist.

If pregnant or breast-feeding, ask a health
professional before use.

Keep out of reach of children. If
swallowed, get medical help or contact a
Poison Control Center right away.

Directions
●See side panel for directions
●Shake before each use
●Pump one spray into each nostril. Use
once every 4 hours.
●Wait at least 30 seconds before blowing
nose.

Inactive Ingredients
Purified water USP, glycerin, hempseed
(cannabis sativa) oil, sodium chloride,
benzyl alcohol, sodium phosphate dibasic
dihydrate, benzalkonium chloride,
potassium chloride, potassium phosphate
monobasic.